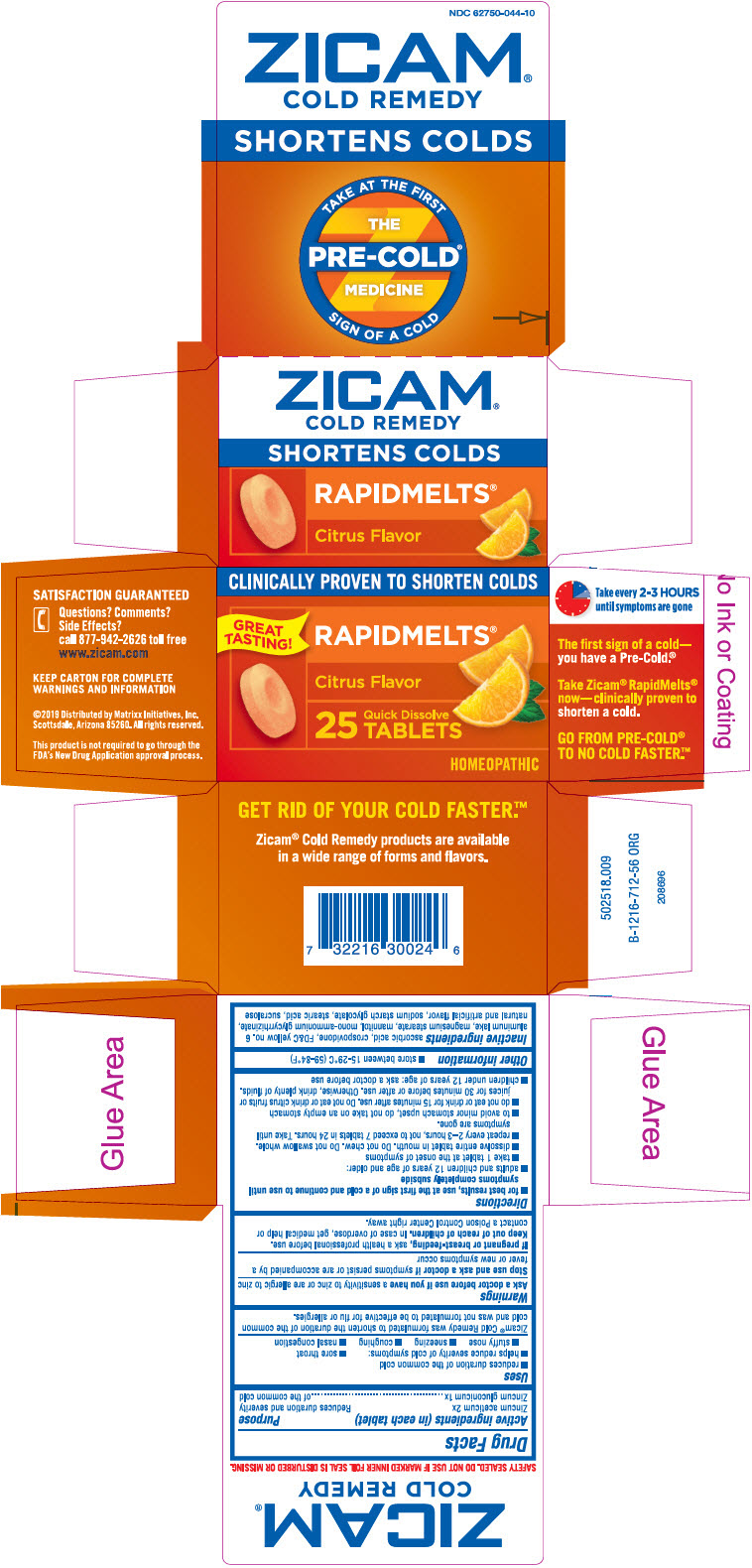 DRUG LABEL: Zicam
NDC: 62750-044 | Form: TABLET
Manufacturer: Matrixx Initiatives, Inc.
Category: homeopathic | Type: HUMAN OTC DRUG LABEL
Date: 20230126

ACTIVE INGREDIENTS: ZINC ACETATE ANHYDROUS 2 [hp_X]/1 1; ZINC GLUCONATE 1 [hp_X]/1 1
INACTIVE INGREDIENTS: ascorbic acid; CROSPOVIDONE (120 .MU.M); FD&C Yellow No. 6; aluminum oxide; magnesium stearate; mannitol; ammonium glycyrrhizate; stearic acid; sucralose; sodium starch glycolate type A potato

Zicam® Cold Remedy Rapidmelts® Citrus

Drug Facts

Active ingredients (in each tablet)

Zincum aceticum 2x
Zincum gluconicum 1x

Purpose

Reduces duration and severity of the common cold

Uses

- reduces duration of the common cold
- helps reduce severity of cold symptoms:
  - sore throat
  - stuffy nose
  - sneezing
  - coughing
  - nasal congestion

Zicam® Cold Remedy was formulated to shorten the duration of the common cold and was not formulated to be effective for flu or allergies.

Warnings

Ask a doctor before use if you have a sensitivity to zinc or are allergic to zinc

Stop use and ask a doctor if symptoms persist or are accompanied by a fever or new symptoms occur

PREGNANCY OR BREAST FEEDING

If pregnant or breast-feeding, ask a health professional before use.

Keep out of reach of children. In case of overdose, get medical help or contact a Poison Control Center right away.

Directions

- for best results, use at the first sign of a cold and continue to use until symptoms completely subside
- adults and children 12 years of age and older:
  - take 1 tablet at the onset of symptoms
  - dissolve entire tablet in mouth. Do not chew. Do not swallow whole.
  - repeat every 2–3 hours, not to exceed 7 tablets in 24 hours. Take until symptoms are gone.
  - to avoid minor stomach upset, do not take on an empty stomach
  - do not eat or drink for 15 minutes after use. Do not eat or drink citrus fruits or juices for 30 minutes before or after use. Otherwise, drink plenty of fluids.
- children under 12 years of age: ask a doctor before use

Other information

- store between 15-29°C (59-84°F)

Inactive ingredients

ascorbic acid, crospovidone, FD&C yellow no. 6 aluminum lake, magnesium stearate, mannitol, mono-ammonium glycyrrhizinate, natural and artificial flavor, sodium starch glycolate, stearic acid, sucralose

Questions? Comments? Side Effects?

call 877-942-2626 toll free

Distributed by Matrixx Initiatives, Inc.
Scottsdale, Arizona 85260.

PRINCIPAL DISPLAY PANEL - 25 Tablet Bottle Carton

CLINICALLY PROVEN TO SHORTEN COLDS

GREAT
TASTING!

RAPIDMELTS®

Citrus Flavor

25
Quick Dissolve
TABLETS

HOMEOPATHIC